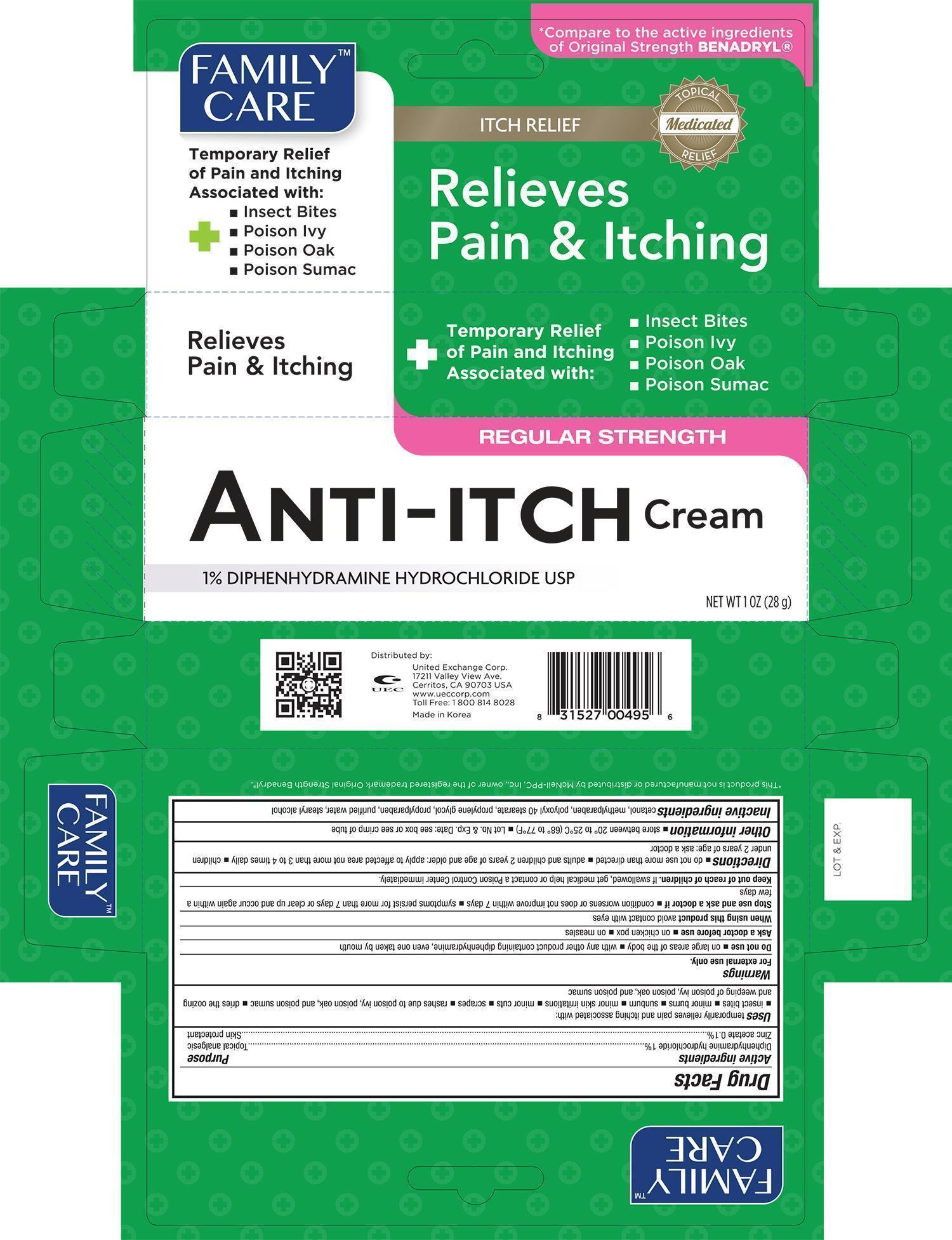 DRUG LABEL: Family Care Anti-Itch
NDC: 65923-495 | Form: CREAM
Manufacturer: United Exchange Corp.
Category: otc | Type: HUMAN OTC DRUG LABEL
Date: 20141124

ACTIVE INGREDIENTS: DIPHENHYDRAMINE HYDROCHLORIDE 1 g/100 g; ZINC ACETATE .1 g/100 g
INACTIVE INGREDIENTS: METHYLPARABEN; POLYOXYL 40 STEARATE; PROPYLENE GLYCOL; PROPYLPARABEN; WATER; STEARYL ALCOHOL

Active Ingredients Purpose

Diphenhydramine hydrochloride 1%................................................ Topical analgesic

Zinc acetate 0.1%........................................................................ Skin protectant

Uses

Temporarily relieves pain and itching associated with:

- insect bites
- minor burns
- sunburn
- minor skin irritations
- minor cuts
- scrapes
- rashes due to poison ivy
- poison oak
- poison sumac
- drise the oozing and weeping of poison ivy, poison oak, and poison sumac

Warnings

For external use only

Do not use

- on large areas of the body
- with any other product containing diphenhydramine, even one taken by mouth

Ask a doctor before use

- on chicken pox
- on measles

When using this product avoid contact with eyes

Stop use and ask a doctor if

- condition worsens or does not improve within 7 days
- symptoms persist for more than 7 days or clear up and occur again within a few days

Keep out of reach of children. If swallowed, get medical help or contact a Poison Control Center immediately

Directions

- do not use more than directed
- adults and children 2 years of age and older: apply to affected area not more than 3 to 4 times daily
- children under 2 years of age: ask a doctor

Other information

- store between 20° to 25°C (68° to 77°F)
- Lot No. & Exp. Date: see box or see crimp of tube

Inactive ingredients

cetanol, methylparaben, polyoxyl 40 stearate, propylene glycol, propylparaben, purified water, stearyl alcohol

DOSAGE AND ADMINISTRATION

Distributed by:

United Exchange Corp.

17211 Valley View Ave.

Cerritos CA 90703 USA

Made in Korea